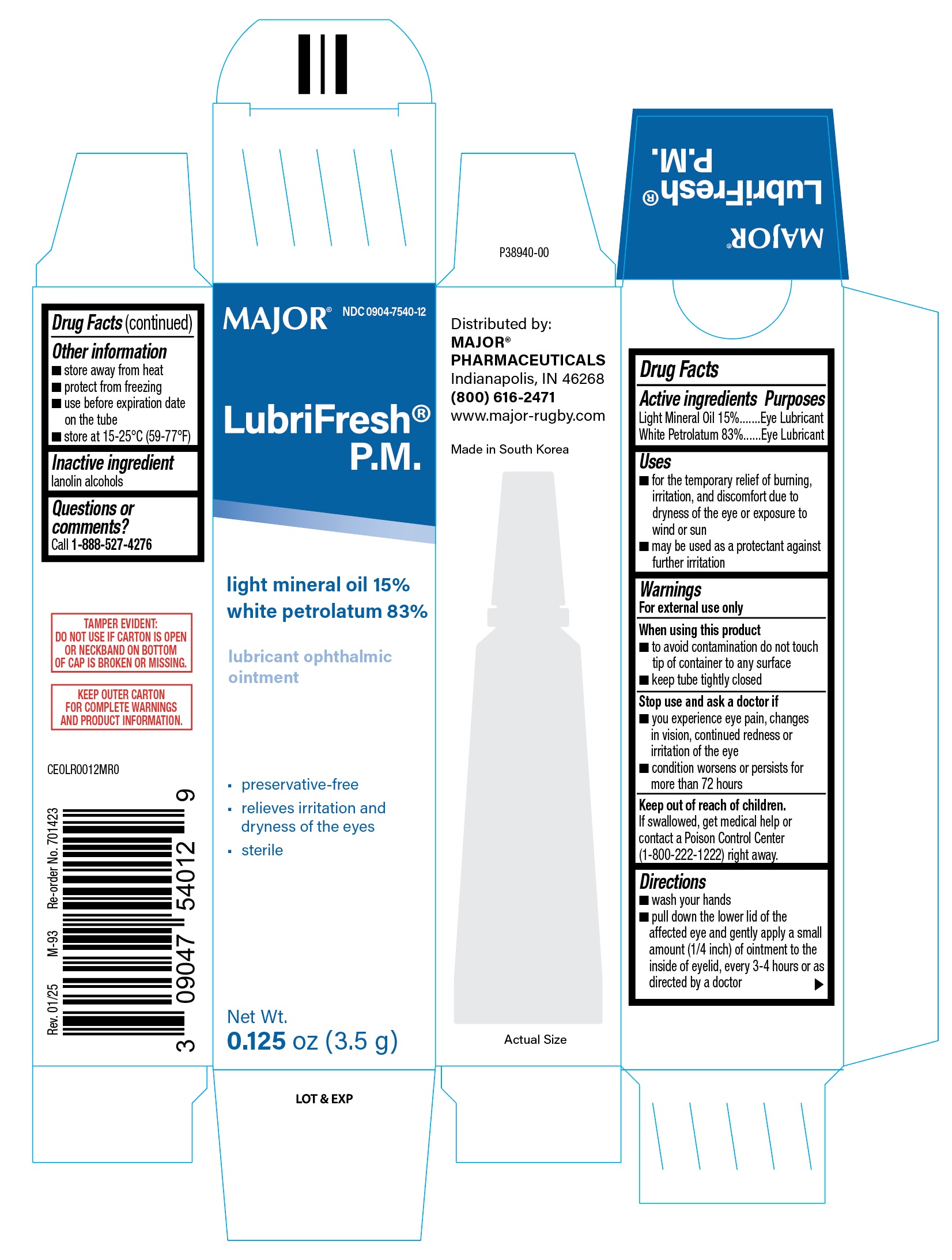 DRUG LABEL: LubriFresh PM
NDC: 11716-7540 | Form: OINTMENT
Manufacturer: Hanlim Pharm Co. , LTD
Category: otc | Type: HUMAN OTC DRUG LABEL
Date: 20250731

ACTIVE INGREDIENTS: LIGHT MINERAL OIL 150 mg/1 g; WHITE PETROLATUM 830 mg/1 g
INACTIVE INGREDIENTS: LANOLIN ALCOHOLS

LubriFresh PM (MFR for PLD)

ACTIVE INGREDIENT

Light Mineral Oil 15%

White Petrolatum 83%

PURPOSE

Eye Lubricant

INDICATIONS AND USAGE

- for the temporary relief of burning, irritation, and discomfort due to dryness of the eye or exposure to wind or sun
- may be used as a protectant against further irritation

DOSAGE AND ADMINISTRATION

- wash your hands
- pull down the lower lid of the affected eye apply a small amount (1/4 inch) of ointment to the inside of eyelid, every 3-4 hours, or as directed by a doctor.

INACTIVE INGREDIENT

lanolin alcohols

Keep out of reach of children.

If swallowed, get medical help or contact a Poison Control Center (1-800-222-1222) right away.

WARNINGS

For external use only

When using this product

- to avoid contamination do not touch tip of container to any surface
- replace cap after use

Stop use and ask a doctor if

- you experience eye pain, changes in vision, continued redness or irritation of the eye
- condition worsens or persists for more than 72 hours

Keep out of reach of children.

If swallowed, get medical help or contact a Poison Control Center (1-800-222-1222) right away.